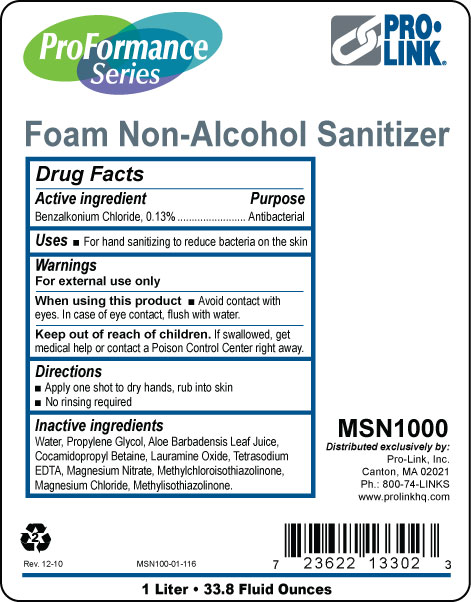 DRUG LABEL: ProFormance Series Foam Non-Alcohol Sanitizer
NDC: 66908-106 | Form: LIQUID
Manufacturer: Pro-Link, Inc.
Category: otc | Type: HUMAN OTC DRUG LABEL
Date: 20101216

ACTIVE INGREDIENTS: Benzalkonium Chloride 0.13 mL/100 mL
INACTIVE INGREDIENTS: WATER; PROPYLENE GLYCOL; ALOE VERA LEAF; COCAMIDOPROPYL BETAINE; LAURAMINE OXIDE; EDETATE SODIUM; MAGNESIUM NITRATE; METHYLCHLOROISOTHIAZOLINONE; MAGNESIUM CHLORIDE; METHYLISOTHIAZOLINONE

Drug Facts

Active ingredient

Benzalkonium Chloride, 0.13%

Purpose

Antibacterial

Uses

For hand sanitizing to reduce bacteria on the skin

Warnings

For external use only

When using this product avoid contact with eyes.

In case of eye contact, flush with water.

Keep out of reach of children.

If swallowed, get medical help or contact a Poison Control Center right away.

Directions

Apply one shot to dry hands, rub into skin

No rinsing required

INACTIVE INGREDIENT

Water, Propylene Glycol, Aloe Barbadensis Leaf Juice, Cocamidopropyl Betaine, Lauramine Oxide, Tetrasodium EDTA, Magnesium Nitrate, Methylchloroisothiazolinone, Magnesium Chloride, Methylisothiazolinone.

PACKAGE LABEL

ProFormance Series

Foam Non-Alcohol Sanitizer

Pro-Link

MSN1000

Distributed exclusively by

Pro-Link, Inc.

1 Liter

33.8 Fluid Ounces